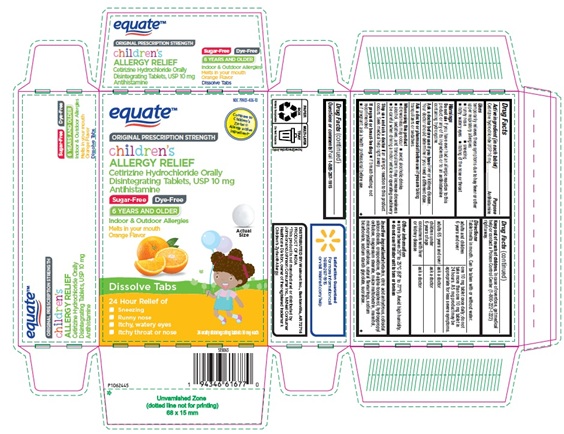 DRUG LABEL: CHILDRENS CETIRIZINE HYDROCHLORIDE
NDC: 79903-406 | Form: TABLET, ORALLY DISINTEGRATING
Manufacturer: WALMART INC.
Category: otc | Type: Human OTC Drug Label
Date: 20260130

ACTIVE INGREDIENTS: CETIRIZINE HYDROCHLORIDE 10 mg/1 1
INACTIVE INGREDIENTS: BETADEX; ANHYDROUS CITRIC ACID; SILICON DIOXIDE; CROSPOVIDONE (35 .MU.M); .ALPHA.-TOCOPHEROL, DL-; HYDROXYPROPYL CELLULOSE (110000 WAMW); MAGNESIUM STEARATE; MALTODEXTRIN; MANNITOL; MICROCRYSTALLINE CELLULOSE 101; MICROCRYSTALLINE CELLULOSE 102; SODIUM BICARBONATE; SODIUM STARCH GLYCOLATE TYPE A POTATO; SUCRALOSE

Drug Facts

Active ingredient (in each tablet)

Cetirizine hydrochloride USP 10 mg

Purpose

Antihistamine

Uses

temporarily relieves these symptoms due to hay fever or other upper respiratory allergies:

- runny nose
- sneezing
- itchy, watery eyes
- itching of the nose or throat

Do not use

if you have ever had an allergic reaction to this product or any of its ingredients or to an antihistamine containing hydroxyzine.

Ask a doctor before use if you have

liver or kidney disease. Your doctor should determine if you need a different dose.

Ask a doctor or pharmacist before use if you are

taking tranquilizers or sedatives.

When using this product

- drowsiness may occur
- avoid alcoholic drinks
- alcohol, sedatives, and tranquilizers may increase drowsiness
- be careful when driving a motor vehicle or operating machinery

Stop use and ask a doctor if

an allergic reaction to this product occurs. Seek medical help right away.

If pregnant or breast-feeding:

- if breast-feeding: not recommended
- if pregnant: ask a health professional before use.

Keep out of reach of children.

In case of overdose, get medical help or contact a Poison Control Center (1-800-222-1222) right away.

Directions

Tablet melts in mouth. Can be taken with or without water.

adults and children 6 years and over | one 10 mg tablet once daily; do not take more than one 10 mg tablet in 24 hours. A 5 mg product may be appropriate for less severe symptoms.
adults 65 years and over | ask a doctor
children under 6 years of age | ask a doctor
consumers with liver or kidney disease | ask a doctor

Other information

- store between 20° to 25°C (68° to 77°F). Avoid high humidity.
- do not use if blister unit is torn or broken

Inactive ingredients

betadex, citric acid anhydrous, colloidal silicon dioxide, crospovidone, dl-alpha-tocopherol, hydroxypropyl cellulose, magnesium stearate, maize maltodextrin, mannitol, microcrystalline cellulose, natural flavourings, sodium bicarbonate, sodium starch glycolate, sucralose.
Questions or comments?
call 1-888-287-1915

DISTRIBUTED BY:

Walmart Inc., Bentonville, AR 72716
PRODUCT OF INDIA

PACKAGE LABEL-PRINCIPAL DISPLAY PANEL -10 mg (24 Orally Disintegrating Tablets) Blister Carton

ORIGINAL PRESCRIPTION STRENGTH

equateTM

NDC 79903-406-10

Compare to
Children's
Zyrtec®
Allergy active
Ingredient*

children's

ALLERGY RELIEF
Cetirizine Hydrochloride Orally
Disintegrating Tablets, USP 10 mg
Antihistamine

Sugar-Free Dye-Free

6 YEARS AND OLDER

Indoor & Outdoor Allergies
Melts in your mouth Actual
Orange Flavor Size

Dissolve Tabs

24 Hour Relief of

- Sneezing
- Runny nose
- Itchy, watery eyes
- Itchy throat or nose

24 orally disintegrating tablets 10 mg each